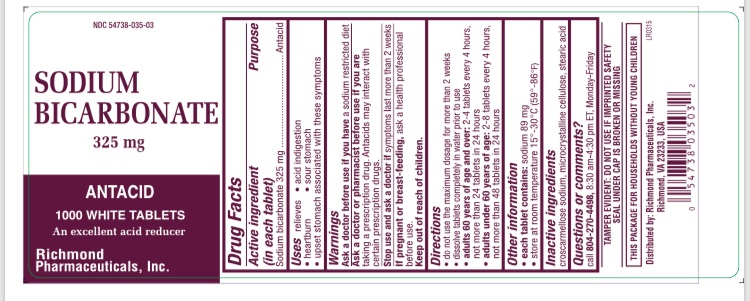 DRUG LABEL: Sodium Bicarbonate Antacid
NDC: 54738-035 | Form: TABLET
Manufacturer: Richmond Pharmaceuticals, Inc.
Category: otc | Type: HUMAN OTC DRUG LABEL
Date: 20171101

ACTIVE INGREDIENTS: SODIUM BICARBONATE 325 mg/1 1
INACTIVE INGREDIENTS: CROSCARMELLOSE SODIUM; CELLULOSE, MICROCRYSTALLINE; STEARIC ACID; SILICON DIOXIDE; TALC

Sodium Bicarbonate 325 mg

Drug Facts

Active ingredient Purpose

(in each tablet)

Sodium bicarbonate 5 gr (325 mg) ....... Antacid

Purpose

Purpose Antacid

Keep out of reach of children

Uses

relieves

- acid indigestion
- heartburn
- sour stomach
- upset stomach associated with these symptoms

Warnings

Ask a doctor before use if you have a sodium restricted diet

Ask a doctor or pharmacist before use of you are

-taking a prescription drug. Antacids may interact with certain prescription drugs.

Stop use and ask a doctor if symptoms last more than 2 weeks

If pregnant or breast-feeding, ask a health professional before use.

This package for households without young children.

Each tablet contains: sodium 89 mg

Directions

- adults 60 years of age and over: 2-4 tablets every 4 hours, not more than 24 tablets in 24 hours
- adults under 60 years of age: 2-8 tablets every 4 hours, not more than 48 tablets in 24 hours
- do not use the maximum dosage for more than 2 weeks
- tablets may be swallowed whole or dissolved in water prior to use

Inactive ingredients

croscarmellose sodium, microcrystalline cellulose, stearic acid

Storage

store at room temperature 15o - 30o C (59o - 86o F)

Questions?

call 804-270-4498, 8.30 am-4.30 pm ET, Monday - Friday
TAMPER EVIDENT: DO NOT USE IF IMPRINTED SAFETY SEAL UNDER CAP IS BROKEN OR MISSING

Principal Display Panel

Sodium Bicarbonate Antacid Tablet

5 gr (325 mg)

1000 White Tablets

NDC- 54738-035-03